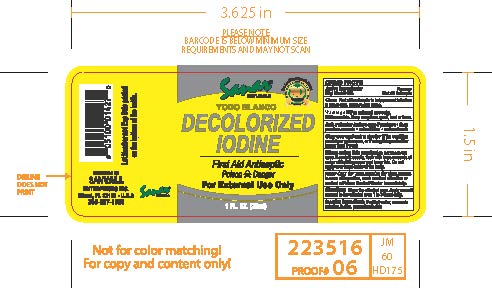 DRUG LABEL: Sanar Naturals Decolorized Iodine
NDC: 73386-147 | Form: LIQUID
Manufacturer: Sanvall Enterprises, Inc
Category: otc | Type: HUMAN OTC DRUG LABEL
Date: 20241031

ACTIVE INGREDIENTS: ALCOHOL 45 mg/1 g
INACTIVE INGREDIENTS: WATER; AMMONIA; IODINE; POTASSIUM IODIDE

Sanar Naturals Decolorized Iodine

Active ingredient

Ethyl Alcohol 45%

Purpose

First Aid Antiseptic

Uses

first aid antiseptic to help prevent infection in minor cuts, scrapes and burns

Warnings

For external use only

Flammable, keep away from spark, heat or flame

Ask a doctor before use

if you have

- deep puncture wounds
- animal bites
- serious burns

Stop use and ask a doctor if

condition persists or gets worse

When using this product

do not use in the eyes. If contact occurs, flush with large amounts of water while lifting upper and lower lids. Donot apply over large areas of the body.

Keep out of reach of children.

In case of ingestion, seek medical attention or contact a Poison Control Center immediately.

Directions

- Clean affected area
- Apply a small amount to the affected area 1 to 3 times daily

Inactive ingredients

Purified water, ammonia solution, iodine, potassium iodide